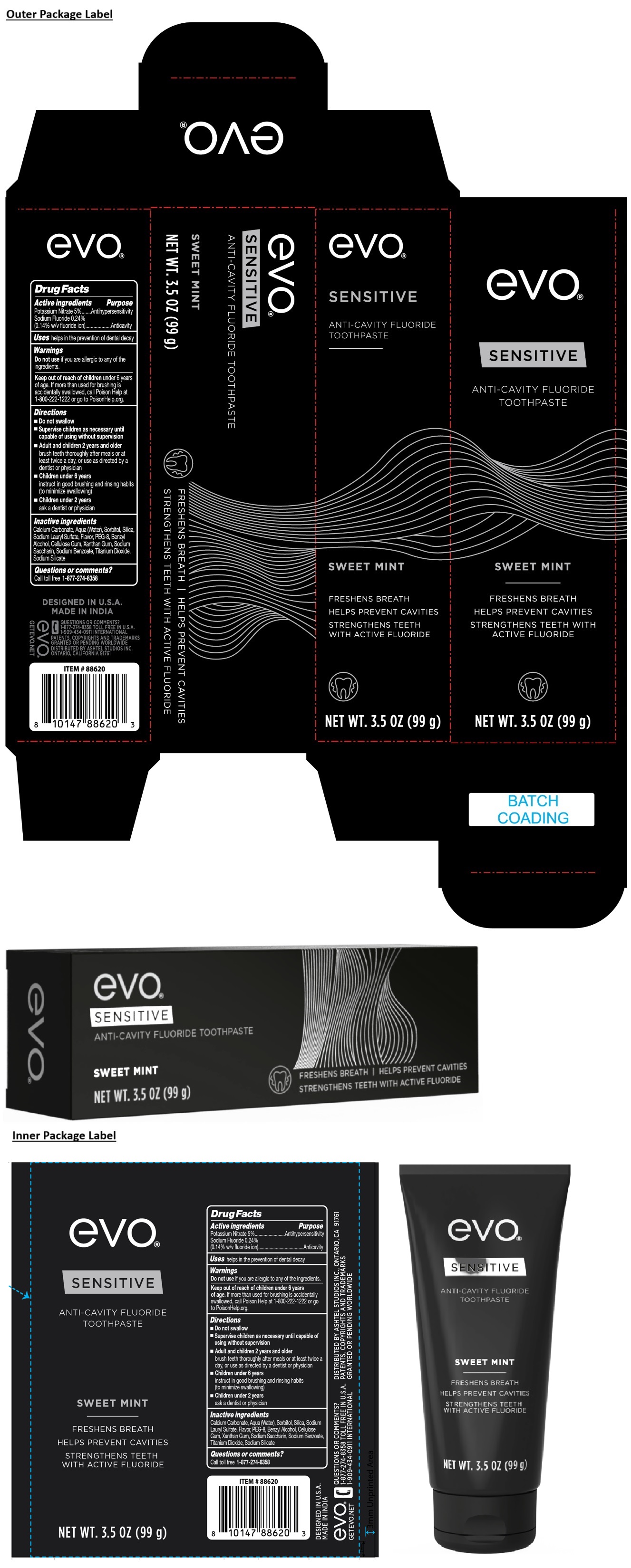 DRUG LABEL: evo SENSITIVE ANTI-CAVITY FLUORIDE SWEET MINT
NDC: 70108-254 | Form: PASTE, DENTIFRICE
Manufacturer: Ashtel Studios, Inc.
Category: otc | Type: HUMAN OTC DRUG LABEL
Date: 20251013

ACTIVE INGREDIENTS: POTASSIUM NITRATE 5 g/100 g; SODIUM FLUORIDE 0.24 g/100 g
INACTIVE INGREDIENTS: CALCIUM CARBONATE; WATER; SORBITOL; SILICON DIOXIDE; SODIUM LAURYL SULFATE; POLYETHYLENE GLYCOL 400; BENZYL ALCOHOL; CARBOXYMETHYLCELLULOSE SODIUM, UNSPECIFIED; XANTHAN GUM; SACCHARIN SODIUM; SODIUM BENZOATE; TITANIUM DIOXIDE; SODIUM SILICATE

evo® SENSITIVE ANTI-CAVITY FLUORIDE TOOTHPASTE SWEET MINT

Active ingredients

Potassium Nitrate 5%
Sodium Fluoride 0.24%
(0.14% w/v fluoride ion)

Purpose

Antihypersensitivity
Anticavity

Uses

helps in the prevention of dental decay

Warnings

Do not use if you are allergic to any of the ingredients.

Keep out of reach of children under 6 years of age. If more than used for brushing is accidentally swallowed, call Poison Help at 1-800-222-1222 or go to PoisonHelp.org.

Directions

• Do not swallow

• Supervise children as necessary until capable of using without supervision

• Adult and children 2 years and older
brush teeth thoroughly after meals or at least twice a day, or use as directed by a dentist or physician

• Children under 6 years
instruct in good brushing and rinsing habits (to minimize swallowing)

• Children under 2 years
ask a dentist or physician

Inactive ingredients

Calcium Carbonate, Aqua (Water), Sorbitol, Silica, Sodium Lauryl Sulfate, Flavor, PEG-8, Benzyl Alcohol, Cellulose Gum, Xanthan Gum, Sodium Saccharin, Sodium Benzoate, Titanium Dioxide, Sodium Silicate

Questions or comments?

Call toll free 1-877-274-8358

FRESHENS BREATH

HELPS PREVENT CAVITIES

STRENGTHENS TEETH WITH ACTIVE FLUORIDE

DESIGNED IN U.S.A.
MADE IN INDIA

GETEVO.NET

1-909-434-0911 INTERNATIONAL

PATENTS, COPYRIGHTS AND TRADEMARKS GRANTED OR PENDING WORLDWIDE
DISTRIBUTED BY ASHTEL STUDIOS INC.
ONTARIO, CALIFORNIA 91761